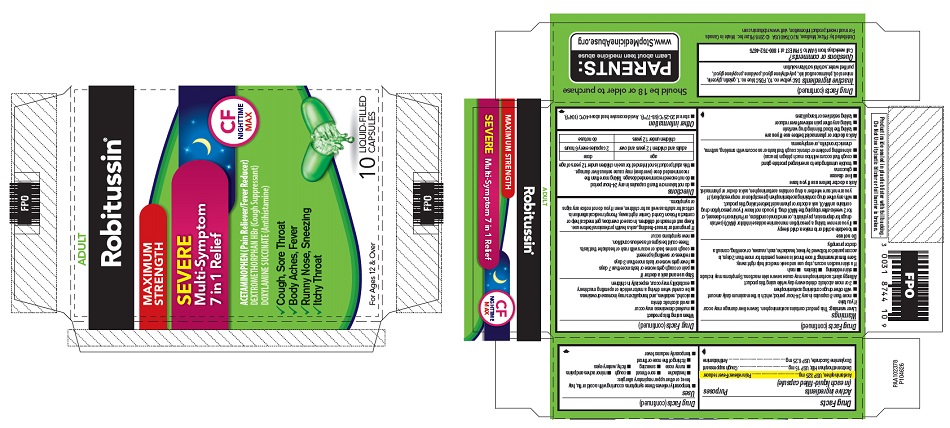 DRUG LABEL: Robitussin Maximum Strength Severe Multi-Symptom 7 in 1 Relief Nighttime
NDC: 0031-8744 | Form: CAPSULE, LIQUID FILLED
Manufacturer: Haleon US Holdings LLC
Category: otc | Type: HUMAN OTC DRUG LABEL
Date: 20240406

ACTIVE INGREDIENTS: ACETAMINOPHEN 325 mg/1 1; DEXTROMETHORPHAN HYDROBROMIDE 15 mg/1 1; DOXYLAMINE SUCCINATE 6.25 mg/1 1
INACTIVE INGREDIENTS: D&C YELLOW NO. 10; FD&C BLUE NO. 1; GELATIN, UNSPECIFIED; GLYCERIN; MINERAL OIL; POLYETHYLENE GLYCOL, UNSPECIFIED; POVIDONE, UNSPECIFIED; PROPYLENE GLYCOL; WATER; SORBITOL

Drug Facts

Active ingredients (in each liquid-filled capsule)

Acetaminophen, USP 325 mg

Dextromethorphan HBr, USP 15 mg

Doxylamine Succinate, USP 6.25 mg

Purposes

Pain reliever/Fever reducer

Cough suppressant

Antihistamine

Uses

- temporarily relieves these symptoms occurring with a cold or flu, hay fever, or other upper respiratory allergies:
  - headache
  - sore throat
  - cough
  - minor aches and pains
  - runny nose
  - sneezing
  - itchy, watery eyes
  - itching of the nose or throat
- temporarily reduces fever

Warnings

Liver warning

This product contains acetaminophen. Severe liver damage may occur if you take

- more than 8 capsules in any 24-hour period, which is the maximum daily amount
- with other drugs containing acetaminophen
- 3 or more alcoholic drinks every day while using this product

Allergy alert:acetaminophen may cause severe skin reactions. Symptoms may include:

- skin reddening
- blisters
- rash

If a skin reaction occurs, stop use and seek medical help right away.

Sore throat warning

If sore throat is severe, persists for more than 2 days, is accompanied or followed by fever, headache, rash, nausea, or vomiting, consult a doctor promptly.

Do not use

- to sedate a child or to make a child sleepy
- if you are now taking a prescription monoamine oxidase inhibitor (MAOI) (certain drugs for depression, psychiatric, or emotional conditions, or Parkinson's disease), or for 2 weeks after stopping the MAOI drug. If you do not know if your prescription drug contains an MAOI, ask a doctor or pharmacist before taking this product.
- with any other drug containing acetaminophen (prescription or nonprescription). If you are not sure whether a drug contains acetaminophen, ask a doctor or pharmacist.

Ask a doctor before use if you have

- liver disease
- glaucoma
- trouble urinating due to an enlarged prostate gland
- cough that occurs with too much phlegm (mucus)
- a breathing problem or chronic cough that lasts or as occurs with smoking, asthma, chronic bronchitis, or emphysema

Ask a doctor or pharmacist before use if you are

- taking the blood thinning drug warfarin
- taking any other pain reliever/fever reducer
- taking sedatives or tranquilizers

When using this product

- marked drowsiness may occur
- avoid alcoholic drinks
- alcohol, sedatives, and tranquilizers may increase drowsiness
- be careful when driving a motor vehicle or operating machinery
- excitability may occur, especially in children

Stop use and ask a doctor if

- pain or cough gets worse or lasts more than 7 days
- fever gets worse or lasts more than 3 days
- redness or swelling is present
- cough comes back or occurs with rash or headache that lasts.
  These could be signs of a serious condition.
- new symptoms occur

PREGNANCY OR BREAST FEEDING

If pregnant or breast-feeding,ask a health professional before use.

Keep out of reach of children.In case of overdose, get medical help or contact a Poison Control Center right away. Prompt medical attention is critical for adults as well as for children, even if you do not notice any signs or symptoms.

Directions

- do not take more than 8 capsules in any 24-hour period
- do not exceed recommended dosage. Taking more than the recommended dose (overdose) may cause serious liver damage.
- this adult product is not intended for use in children under 12 years of age

age | dose
adults and children 12 years and over | 2 capsules every 6 hours
children under 12 years | do not use

Other information

- store at 20-25°C (68-77°F). Avoid excessive heat above 40°C (104°F).

Inactive ingredients

D&C yellow no. 10, FD&C blue no. 1, gelatin, glycerin, mineral oil, pharmaceutical ink, polyethylene glycol, povidone, propylene glycol, purified water, sorbitol sorbitan solution

Questions or comments?

Call weekdays from 9 AM to 5 PM EST at 1 800-762-4675

Distributed by: Pfizer, Madison, NJ 07940 USA

PRINCIPAL DISPLAY PANEL

ADULT

Robitussin®

- MAXIMUM
  STRENGTH
- SEVERE
  Multi-Symptom
  7 in 1 Relief

ACETAMINOPHEN (Pain Reliever/Fever Reducer)
DEXTROMETHORPHAN HBr (Cough Suppressant)
DOXYLAMINE SUCCINATE (Antihistamine)

CF
NIGHTTIME
MAX

1. Cough, Sore Throat
2. Body Aches, Fever
3. Runny Nose, Sneezing
4. Itchy Throat

For Ages 12 & Over

10
LIQUID-FILLED
CAPSULES